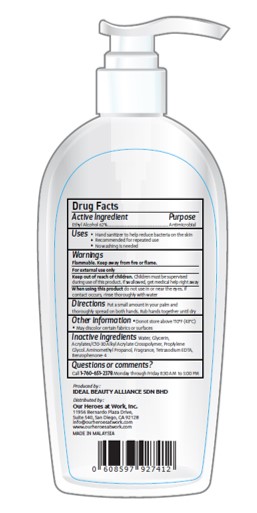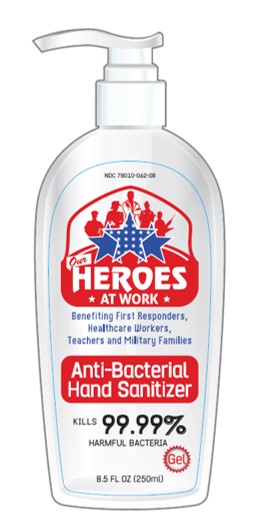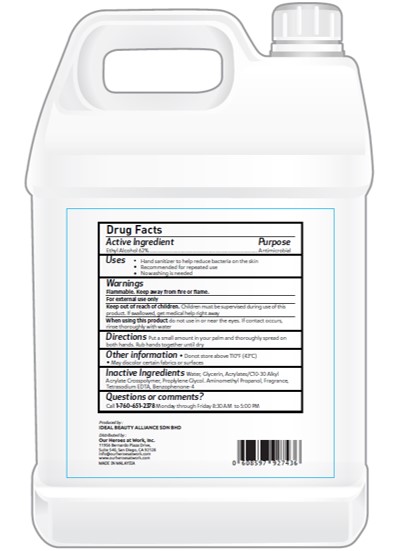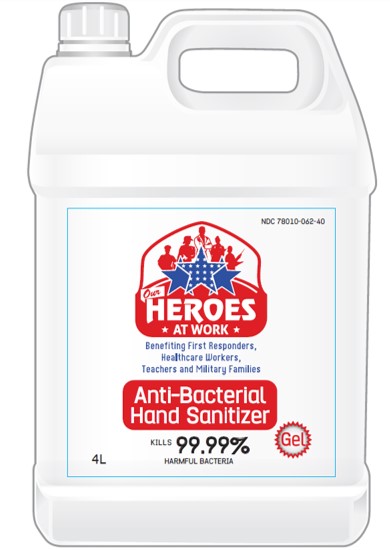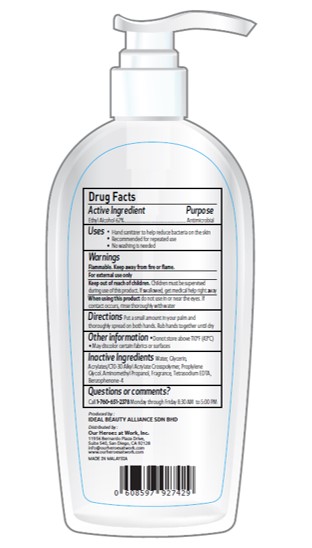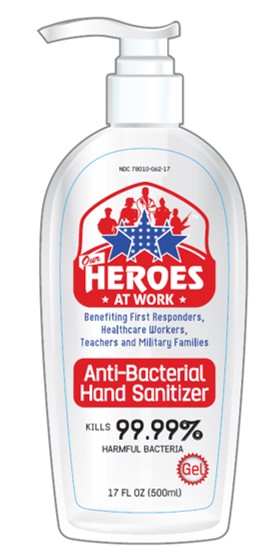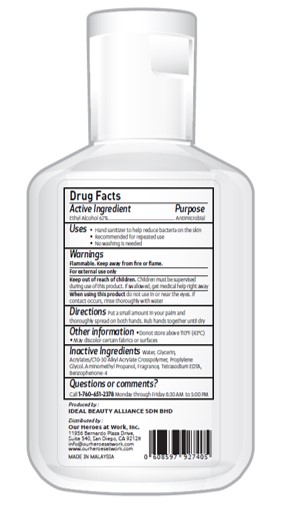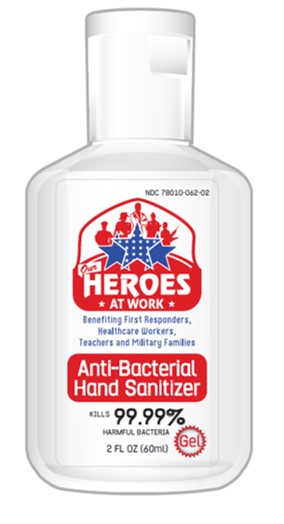 DRUG LABEL: Hand Sanitizer
NDC: 78010-062 | Form: GEL
Manufacturer: IDEAL BEAUTY ALLIANCE SDN. BHD.
Category: otc | Type: HUMAN OTC DRUG LABEL
Date: 20200518

ACTIVE INGREDIENTS: ALCOHOL 62.4 mL/100 mL
INACTIVE INGREDIENTS: WATER 32.69 mL/100 mL; PROPYLENE GLYCOL 0.8 mL/100 mL; GLYCERIN 2 mL/100 mL; AMINOMETHYLPROPANOL 0.8 mL/100 mL

Hand Sanitizer

Active Ingredients

Ethyl Alcohol 62.4% v/v. Purpose: Antimicrobial

Purpose

Antimicrobial, Hand Sanitizer

Warnings

For External Use Only

When using this product do not us in or near the eyes. If contact occurs, rinse thoroughly with water.

WARNINGS

Flammable. Keep away from fire or flame.

Stop use and ask a doctor if irritation or rash appears and lasts.

Keep out of reach of children.

Children must be supervised in use of this product. If swallowed get medical help right away.

Inactive Ingredients

Water, Glycerin, Acrylates /C10-30 Alkyl Acrylate Crosspolymer, Propylene Glycol, Aminomethyl Propanol, Fragrance, Tetrasodium EDTA, Benzophenone-4

Directions

Put a small amount in your palm and thoroughly spread on both hands. Rub hands together until dry

Uses

- Hand Sanitizer to help reduce bacteria on the skin=
- Recommended for repeated use
- No washing is needed

Other Information

- Do not store above 110°F (43°C).
- May discolor certain fabrics or surfaces.